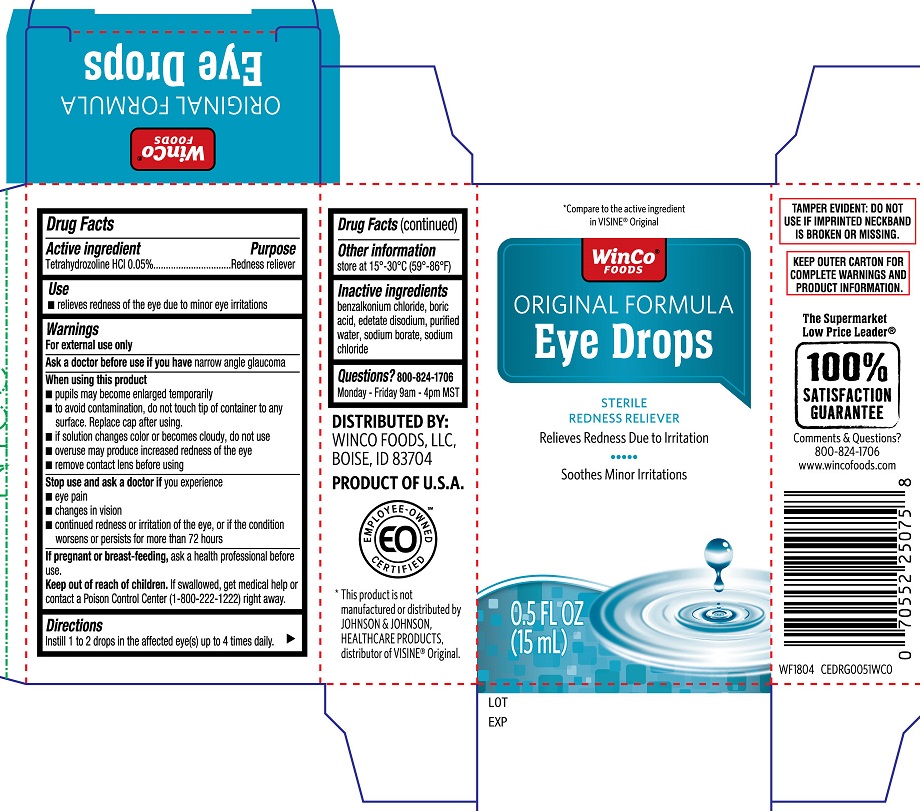 DRUG LABEL: Winco Original Formula Eye Drops
NDC: 67091-310 | Form: SOLUTION/ DROPS
Manufacturer: WinCo Foods, LLC
Category: otc | Type: HUMAN OTC DRUG LABEL
Date: 20251230

ACTIVE INGREDIENTS: TETRAHYDROZOLINE HYDROCHLORIDE 0.05 g/100 mL
INACTIVE INGREDIENTS: BENZALKONIUM CHLORIDE; BORIC ACID; EDETATE DISODIUM; WATER; SODIUM BORATE; SODIUM CHLORIDE

Winco Original Formula Eye Drops 15 mL (PLD)

Active ingredient

Tetrahydrozoline HCL 0.05%

Purpose

Redness reliever

Uses

- relieves redness of the eye due to minor eye irritations

Warnings

For external use only

Ask a doctor before use if you have

narrow angle glaucoma

When using this product

- pupils may become enlarged temporarily
- to avoid contamination, do not touch tip of container to any surface. Replace cap after using
- if solution changes color or becomes cloudy, do not use
- overuse may produce increased redness of the eye
- remove contact lens before using

Stop use and ask a doctor if

you experience

- eye pain
- changes in vision
- continued redness or irritation of the eye, or if the condition worsens or persists for more than 72 hours

If pregnant or breast-feeding

ask a health professional before use

Keep out of reach of chlidren

If swallowed, get medical help or contact a Poison Control Center (1-800-222-1222) right away.

Directions

Instill 1 or 2 drops in the affected eye(s) up to four times daily

Other information

store at 15-30°C (59°-86°F)

Inactive ingredients

benzalkonium chloride, boric acid, edetate disodium, purified water, sodium borate, sodium chloride